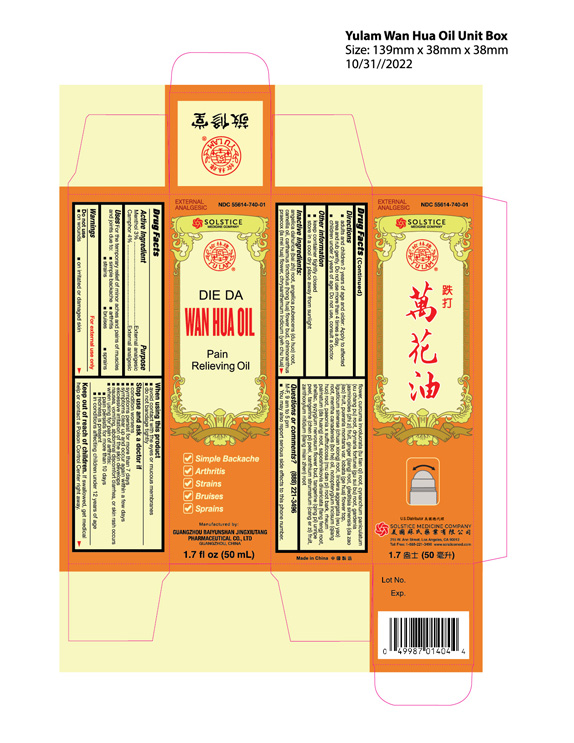 DRUG LABEL: YULAM DIE DA WAN HUA PAIN RELIEVING
NDC: 55614-740 | Form: OIL
Manufacturer: MADISON ONE ACME INC
Category: otc | Type: HUMAN OTC DRUG LABEL
Date: 20251112

ACTIVE INGREDIENTS: MENTHOL 3 g/100 mL; CAMPHOR (SYNTHETIC) 4 g/100 mL
INACTIVE INGREDIENTS: ANGELICA DAHURICA ROOT; ANGELICA PUBESCENS ROOT; CAMELLIA OIL; CARTHAMUS TINCTORIUS FLOWER BUD; CHIMONANTHUS PRAECOX WHOLE; CHRYSANTHEMUM INDICUM FLOWER; CURCUMA INVOLUCRATA ROOT; CYNANCHUM PANICULATUM ROOT; DRYNARIA FORTUNEI ROOT; GARDENIA JASMINOIDES FRUIT; GINGER; GLEDITSIA SINENSIS FRUIT; PUERARIA MONTANA VAR. LOBATA FLOWERING TOP; LIGUSTICUM SINENSE ROOT; LINDERA AGGREGATA ROOT; MENTHA CANADENSIS WHOLE; NOTOPTERYGIUM INCISUM ROOT; PAEONIA X SUFFRUTICOSA ROOT BARK; RHEUM PALMATUM ROOT; SAPOSHNIKOVIA DIVARICATA ROOT; SHELLAC; SYZYGIUM NERVOSUM FLOWER BUD; TANGERINE PEEL, UNRIPE; TANGERINE PEEL; XANTHIUM STRUMARIUM FRUIT; ZANTHOXYLUM NITIDUM ROOT

Drug Facts

Active ingredient
Menthol 3%
Camphor 4%

Purpose
External analgesic
External analgesic

Uses
For the temporary relief of minor aches and pains of muscles and joints due to:
■ simple backache
■ arthritis
■ strains
■ bruises
■ sprains

Warnings
For external use only

Do not use
■ on wounds
■ on irritated or damaged skin

When using this product
■ avoid contact with the eyes or mucous membranes
■ do not bandage tightly

Stop use and ask a doctor if
■ condition worsens
■ symptoms persist for more than 7 days
■ symptoms clear up and occur again within a few days
■ excessive irritation of the skin develops
■ nausea, vomiting, abdominal discomfort, diarrhea, or skin rash occurs
■ when using for pain of arthritis:
■ pain persists for more than 10 days
■ redness is present
■ in conditions affecting children under 12 years of age

ADVERSE REACTIONS

Report any unexpected side effectsfrom the use of this product to the FDA MedWatch Program.

KEEP OUT OF REACH OF CHILDREN

Keep out of reach of childrento avoid accidental poisoning. If swallowed, get medical help or contact a Poison Control Center right away.

Directions
■ adults and children 2 years of age and older: Apply to affected area and rub gently. Do not use for more than 4 times a day.
■ children under 2 years of age: Do not use, consult a doctor.

Other information
■ keep container tightly closed
■ store in a cool dry place away from sunlight

INACTIVE INGREDIENT

Inactive ingredientsangelica dahurica (bai zhi) root, angelica pubescens (du huo) root, camellia oil, carthamus tinctorius (hong hua) flower bud, chimonanthus praecox (la mei hua) flower, chrysanthemum indicum (yeh chu hua) flower, curcuma involucrata (tu tian qi) root, cynanchum paniculatum (xu chang pu) root, drynaria fortunei (gu sui bu) root, gardenia jasminoides (zhi zi) fruit, ginger (jiang) root, gleditsia sinensis (da zao jiao) fruit, pueraria montana var. lobata (ge hua) flower top, ligusticum sinense (chuan xiong) root, lindera aggergata (wu yao) root, mentha canadensis (bo he) oil, notopterygium incisum (qiang huo) root, paeonia x suffruticosa (mu dan pi) root bark, rheum palmatum (da huang) root, saposhnikovia divaricata (fang feng) root, shellac, syzygium nervosum flower bud, tangerine (qing pi) unripe peel, tangerine (chen pi) peel, xanthium strumarium (cang er zi) fruit, zanthoxylum nitidum (liang mian zhen) root.

Questions or comments? (888) 221-3496M-F 9 am to 5 pm
■ you may also report serious side effects to this phone number

PACKAGE LABEL

YULAM DIE DA WAN HUA PAIN RELIEVING OIL

NDC 55614-740-01

EXTERNAL ANALGESIC

1.7 FL OZ (50 ML)